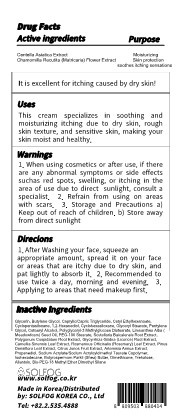 DRUG LABEL: Sol Ato24 Calming Moisture Cream
NDC: 84077-302 | Form: LOTION
Manufacturer: SOLFOG KOREA Co., Ltd
Category: otc | Type: HUMAN OTC DRUG LABEL
Date: 20240307

ACTIVE INGREDIENTS: CHAMOMILE 0.5 g/100 g; CENTELLA ASIATICA 0.5 g/100 g
INACTIVE INGREDIENTS: PROPANEDIOL; XANTHAN GUM; CARBOXYMETHYLCELLULOSE SODIUM; CYCLOMETHICONE; ROSEMARY; POLYGLYCERYL-3 METHYLGLUCOSE DISTEARATE; GLYCERYL MONOSTEARATE; BUTYLENE GLYCOL; PANTHENOL; EDETATE DISODIUM; FD&C YELLOW NO. 5; CENTELLA ASIATICA TRITERPENOIDS; CETYL ETHYLHEXANOATE; ARTEMISIA ANNUA FLOWERING TOP; ISOHEXADECANE; SHEA BUTTER; FRAGRANCE 13576; PINUS DENSIFLORA LEAF; CITRUS JUNOS FRUIT; WATER; MEADOWFOAM SEED OIL; SCUTELLARIA BAICALENSIS ROOT; ALLANTOIN; BIS-PEG-18 METHYL ETHER DIMETHYL SILANE; FD&C BLUE NO. 1; GLYCERIN; GLYCERYL STEARATE SE; CETOSTEARYL ALCOHOL; TREHALOSE; GLYCYRRHIZA GLABRA; MEDIUM-CHAIN TRIGLYCERIDES; POLYGONUM CUSPIDATUM ROOT; GREEN TEA LEAF; DIMETHYL SULFONE; 1,2-HEXANEDIOL; PENTYLENE GLYCOL; PEG-100 STEARATE; DIMETHICONE; SODIUM ACRYLATE/SODIUM ACRYLOYLDIMETHYLTAURATE COPOLYMER (4000000 MW)

84077-302 Sol-Ato24 Calming Moisture Cream

Active Ingredients

Centella Asiatica Extract
Chamomilla Recutita (Matricaria) Flower Extract

Purposes

Moisturizing
skin protection
soothes itching sensations

Uses

This cream specializes in soothing and moisturizing itching due to dry skin, rough skin texture, and sensitive skin, making your
skin moist and healthy.

Warnings

Storage and Precautions a) Keep out of reach of children

Warnings

When using cosmetics or after use, if there are any abnormal symptoms or side effects suchas red spots, swelling, or itching in the
area of use due to direct sunlight, consult a specialist.

Warnings

1. When using cosmetics or after use, if there are any abnormal symptoms or side effects suchas red spots, swelling, or itching in the
area of use due to direct sunlight, consult a specialist.

2. Refrain from using on areas with scars.

3. Storage and Precautions a) Keep out of reach of children, b) Store away from direct sunlight

Directions

1. After Washing your face, squeeze an appropriate amount, spread it on your face or areas that are itchy due to dry skin, and pat lightly to absorb it.

2. Recommended to use twice a day, morning and evening.

3. Applying to areas that need makeup first.

Inactive Ingredients

Water
Glycerin

allantoin
Butylene Glycol
Caprylic/Capric Triglyceride
Cetyl Ethylhexanoate
Cyclopentasiloxane
1,2-Hexanediol
Cyclohexasiloxane
Glyceryl Stearate
Pentylene Glycol
Cetearyl Alcohol
Polyglyceryl-3 Methylglucose Distearate
Limnanthes Alba (Meadowfoam) Seed Oil
PEG-100 Stearate
Scutellaria Baicalensis Root Extract
Polygonum Cuspidatum Root Extract
Glycyrrhiza Glabra (Licorice) Root Extract
Camellia Sinensis Leaf Extract
Rosmarinus Officinalis (Rosemary) Leaf Extract
Pinus Densiflora Leaf Extract
Citrus Junos Fruit Extract
Artemisia Annua Extract
Propanediol
Sodium Acrylate/Sodium Acryloyldimethyl Taurate Copolymer
Isohexadecane
Butyrospermum Parkii (Shea) Butter
Dimethicone
Trehalose
Bis-PEG-18 Methyl Ether Dimethyl Silane
Panthenol
Xanthan Gum
Cellulose Gum
Disodium EDTA
Dimethyl Sulfone
CI 19140
CI 42090
Fragrance

Label